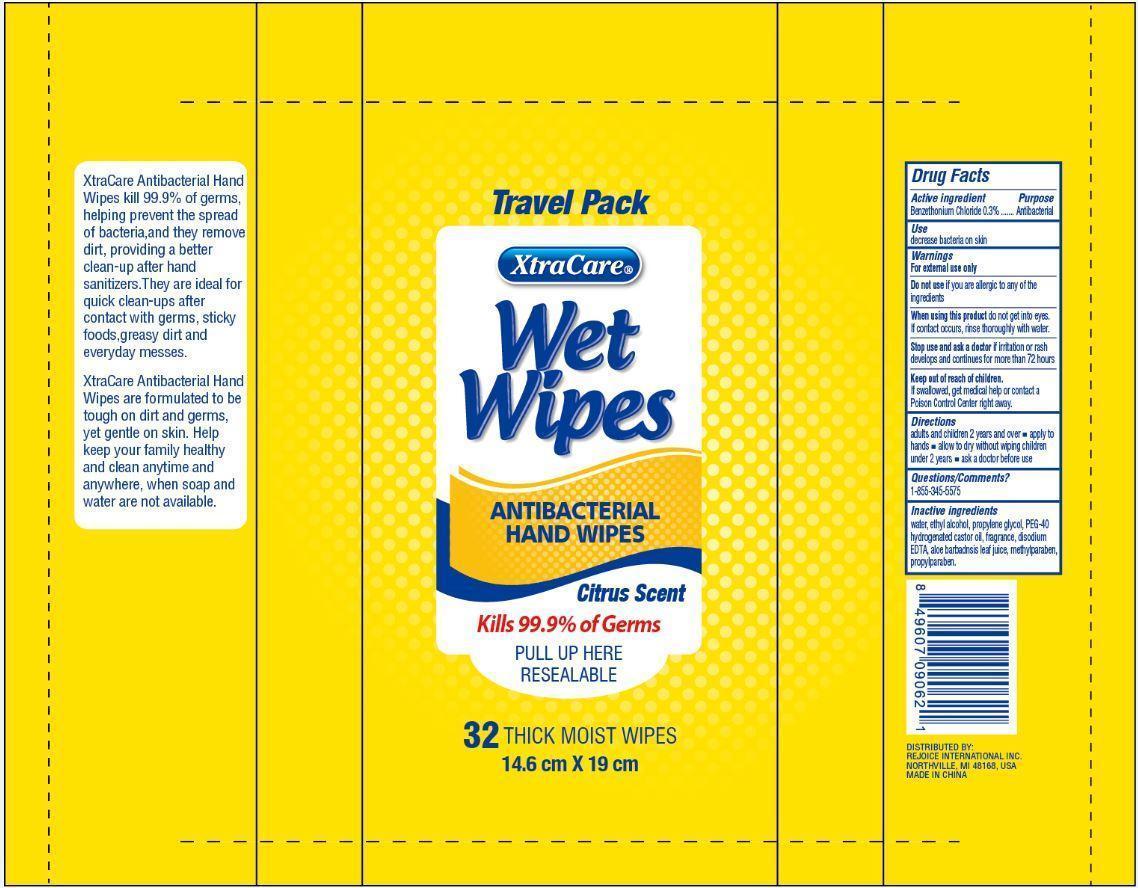 DRUG LABEL: Wet Wipes
NDC: 57337-066 | Form: CLOTH
Manufacturer: Rejoice International
Category: otc | Type: HUMAN OTC DRUG LABEL
Date: 20250212

ACTIVE INGREDIENTS: BENZETHONIUM CHLORIDE 0.3 g/1 1
INACTIVE INGREDIENTS: WATER; ALCOHOL; PROPYLENE GLYCOL; POLYOXYL 40 HYDROGENATED CASTOR OIL; EDETATE DISODIUM; ALOE VERA LEAF; METHYLPARABEN; PROPYLPARABEN

Wet Wipes

Active Ingredient Purpose

Benzethonium Chloride 0.3% ............... Antibacterial

Uses

decrease bacteria on skin

Keep out of reach of children. If swallowed, get medical help or contact a Poison Control Center right away.

INDICATIONS AND USAGE

XtraCare Wet Wipes

Antibacterial Hand Wipes

Citrus Scent

Kills 99.9% of germs

Pull up here

Resealable

32 Thick Moist Wipes

14.6 cm x 19 cm

XtraCare Antibacterial Hand Wipes kill 99.9% of germs, helping prevent the spread of bacteria, and they remove dirt, providing a better clean-up after hand sanitizers. They are ideal for quick clean-ups after contact with germs, sticky foods, greasy dirt and everyday messes.

XtraCare Antibacterial Hand Wipes are formulated to be tough on dirt and germs, yet gentle on skin. Help keep your family healthy and clean anytime and anywhere, when soap and water are not available.

Warnings

For external use only

Do not use if you are allergic to any of the ingredients

When using this product do not get into eyes. If contact occurs, rinse thoroughly with water.

Stop use and ask a doctor if irritation or rash develops and continues for more than 72 hours.

Directions

adults and children 2 years and over

- apply to hands
- allow to dry without wiping

children under 2 years

- ask a doctor before use

Inactive Ingredients

water, ethyl alcohol, propylene glycol, PEG-40 hydrogenated castor oil, fragrance, disodium EDTA, aloe barbadensis leaf juice, methylparaben, propylparaben.